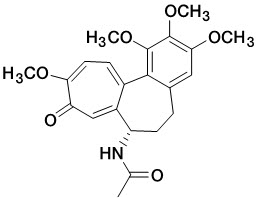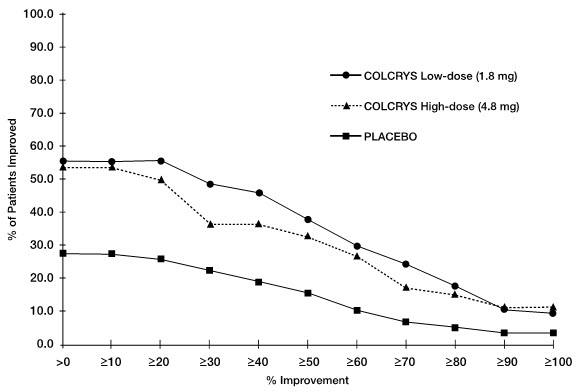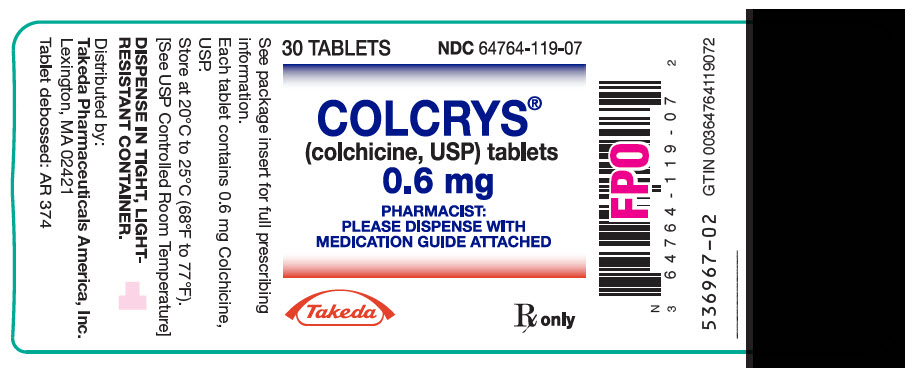 DRUG LABEL: Colcrys
NDC: 64764-119 | Form: TABLET, FILM COATED
Manufacturer: Takeda Pharmaceuticals America, Inc.
Category: prescription | Type: HUMAN PRESCRIPTION DRUG LABEL
Date: 20250723

ACTIVE INGREDIENTS: Colchicine 0.6 mg/1 1
INACTIVE INGREDIENTS: carnauba wax; FD&C blue no. 2; FD&C red no. 40; HYPROMELLOSE, UNSPECIFIED; lactose monohydrate; magnesium stearate; MICROCRYSTALLINE CELLULOSE; polydextrose; POLYETHYLENE GLYCOL, UNSPECIFIED; starch, corn; sodium starch glycolate type A potato; titanium dioxide; triacetin

HIGHLIGHTS OF PRESCRIBING INFORMATION

These highlights do not include all the information needed to use colchicine safely and effectively. See full prescribing information for COLCRYS.
COLCRYS (colchicine, USP) tablets, for oral use
Initial U.S. Approval: 1961

1 INDICATIONS AND USAGE

COLCRYS (colchicine, USP) is an alkaloid indicated for:

- Prophylaxis and treatment of gout flares in adults (1.1).
- Familial Mediterranean fever (FMF) in adults and children 4 years or older (1.2).

2 DOSAGE AND ADMINISTRATION

- Gout Flares:
  Prophylaxis of Gout Flares: 0.6 mg once or twice daily in adults and adolescents older than 16 years of age (2.1). Maximum dose 1.2 mg/day.
  Treatment of Gout Flares: 1.2 mg (two tablets) at the first sign of a gout flare followed by 0.6 mg (one tablet) one hour later (2.1).
- FMF: Adults and children older than 12 years 1.2 – 2.4 mg; children 6 to 12 years 0.9 – 1.8 mg; children 4 to 6 years 0.3 – 1.8 mg (2.2, 2.3).
  - Give total daily dose in one or two divided doses (2.2).
  - Increase or decrease the dose as indicated and as tolerated in increments of 0.3 mg/day, not to exceed the maximum recommended daily dose (2.2).
- Colchicine tablets are administered orally without regard to meals.
- See full prescribing information (FPI) for dose adjustment regarding patients with impaired renal function (2.5), impaired hepatic function (2.6), the patient's age (2.3, 8.5) or use of coadministered drugs (2.4).

3 DOSAGE FORMS AND STRENGTHS

Tablets: 0.6 mg colchicine (3)

4 CONTRAINDICATIONS

Patients with renal or hepatic impairment should not be given COLCRYS in conjunction with P-gp or strong CYP3A4 inhibitors (5.3). In these patients, life-threatening and fatal colchicine toxicity has been reported with colchicine taken in therapeutic doses (7).

5 WARNINGS AND PRECAUTIONS

- Fatal overdoses have been reported with colchicine in adults and children. Keep COLCRYS out of the reach of children (5.1, 10).
- Blood dyscrasias: myelosuppression, leukopenia, granulocytopenia, thrombocytopenia and aplastic anemia have been reported (5.2).
- Monitor for toxicity and if present consider temporary interruption or discontinuation of colchicine (5.2, 5.3, 5.4, 6, 10).
- Drug interaction P-gp and/or CYP3A4 inhibitors: Coadministration of colchicine with P-gp and/or strong CYP3A4 inhibitors has resulted in life-threatening interactions and death (5.3, 7).
- Neuromuscular toxicity: Myotoxicity including rhabdomyolysis may occur, especially in combination with other drugs known to cause this effect. Consider temporary interruption or discontinuation of COLCRYS (5.4, 7).

6 ADVERSE REACTIONS

- Prophylaxis of Gout Flares: The most commonly reported adverse reaction in clinical trials for the prophylaxis of gout was diarrhea.
- Treatment of Gout Flares: The most common adverse reactions reported in the clinical trial for gout were diarrhea (23%) and pharyngolaryngeal pain (3%).
- FMF: Most common adverse reactions (up to 20%) are abdominal pain, diarrhea, nausea and vomiting. These effects are usually mild, transient and reversible upon lowering the dose (6).

To report SUSPECTED ADVERSE REACTIONS, contact Takeda Pharmaceuticals America, Inc. at 1-877-TAKEDA-7 (1-877-825-3327) or FDA at 1-800-FDA-1088 or www.fda.gov/medwatch.

7 DRUG INTERACTIONS

Coadministration of P-gp and/or CYP3A4 inhibitors (e.g., clarithromycin or cyclosporine) have been demonstrated to alter the concentration of colchicine. The potential for drug-drug interactions must be considered prior to and during therapy. See FPI for a complete list of reported and potential interactions (2.4, 5.3, 7).

8 USE IN SPECIFIC POPULATIONS

- In the presence of mild to moderate renal or hepatic impairment, adjustment of dosing is not required for treatment of gout flare, prophylaxis of gout flare and FMF, but patients should be monitored closely (8.6).
- In patients with severe renal impairment for prophylaxis of gout flares, the starting dose should be 0.3 mg/day for gout flares, no dose adjustment is required, but a treatment course should be repeated no more than once every two weeks. In FMF patients, start with 0.3 mg/day, and any increase in dose should be done with close monitoring (8.6).
- In patients with severe hepatic impairment, a dose reduction may be needed in prophylaxis of gout flares and FMF patients; while a dose reduction may not be needed in gout flares, a treatment course should be repeated no more than once every two weeks (8.6, 8.7).
- For patients undergoing dialysis, the total recommended dose for prophylaxis of gout flares should be 0.3 mg given twice a week with close monitoring. For treatment of gout flares, the total recommended dose should be reduced to 0.6 mg (one tablet) × 1 dose and the treatment course should not be repeated more than once every two weeks. For FMF patients, the starting dose should be 0.3 mg/day and dosing can be increased with close monitoring 8.6).
- Females and Males of Reproductive Potential: Advise males that COLCRYS may transiently impair fertility (8.3).
- Geriatric Use: The recommended dose of colchicine should be based on renal function (8.5).

FULL PRESCRIBING INFORMATION

1 INDICATIONS AND USAGE

1.1 Gout Flares

COLCRYS (colchicine, USP) tablets are indicated for prophylaxis and the treatment of acute gout flares.

- Prophylaxis of Gout Flares:
  COLCRYS is indicated for prophylaxis of gout flares.
- Treatment of Gout Flares:
  COLCRYS tablets are indicated for treatment of acute gout flares when taken at the first sign of a flare.

1.2 Familial Mediterranean Fever (FMF)

COLCRYS (colchicine, USP) tablets are indicated in adults and children four years or older for treatment of familial Mediterranean fever (FMF).

2 DOSAGE AND ADMINISTRATION

The long-term use of colchicine is established for FMF and the prophylaxis of gout flares, but the safety and efficacy of repeat treatment for gout flares has not been evaluated. The dosing regimens for COLCRYS are different for each indication and must be individualized.

The recommended dosage of COLCRYS depends on the patient's age, renal function, hepatic function and use of coadministered drugs [see Dosage and Administration (2.4, 2.5, 2.6)].

COLCRYS tablets are administered orally without regard to meals.

COLCRYS is not an analgesic medication and should not be used to treat pain from other causes.

2.1 Gout Flares

Prophylaxis of Gout Flares

The recommended dosage of COLCRYS for prophylaxis of gout flares for adults and adolescents older than 16 years of age is 0.6 mg once or twice daily. The maximum recommended dose for prophylaxis of gout flares is 1.2 mg/day.

An increase in gout flares may occur after initiation of uric acid-lowering therapy, including pegloticase, febuxostat and allopurinol, due to changing serum uric acid levels resulting in mobilization of urate from tissue deposits. COLCRYS is recommended upon initiation of gout flare prophylaxis with uric acid-lowering therapy. Prophylactic therapy may be beneficial for at least the first six months of uric acid-lowering therapy.

Treatment of Gout Flares

The recommended dose of COLCRYS for treatment of a gout flare is 1.2 mg (two tablets) at the first sign of the flare followed by 0.6 mg (one tablet) one hour later. Higher doses have not been found to be more effective. The maximum recommended dose for treatment of gout flares is 1.8 mg over a 1-hour period. COLCRYS may be administered for treatment of a gout flare during prophylaxis at doses not to exceed 1.2 mg (two tablets) at the first sign of the flare followed by 0.6 mg (one tablet) one hour later. Wait 12 hours and then resume the prophylactic dose.

2.2 FMF

The recommended dosage of COLCRYS for FMF in adults is 1.2 mg to 2.4 mg daily.

COLCRYS should be increased as needed to control disease and as tolerated in increments of 0.3 mg/day to a maximum recommended daily dose. If intolerable side effects develop, the dose should be decreased in increments of 0.3 mg/day. The total daily COLCRYS dose may be administered in one to two divided doses.

2.3 Recommended Pediatric Dosage

Prophylaxis and Treatment of Gout Flares

COLCRYS is not recommended for pediatric use in prophylaxis or treatment of gout flares.

FMF

The recommended dosage of COLCRYS for FMF in pediatric patients 4 years of age and older is based on age. The following daily doses may be given as a single or divided dose twice daily:

- Children 4 to 6 years: 0.3 mg to 1.8 mg daily
- Children 6 to 12 years: 0.9 mg to 1.8 mg daily
- Adolescents older than 12 years: 1.2 mg to 2.4 mg daily

2.4 Dose Modification for Coadministration of Interacting Drugs

Concomitant Therapy

Coadministration of COLCRYS with drugs known to inhibit CYP3A4 and/or P-glycoprotein (P-gp) increases the risk of colchicine-induced toxic effects (Table 1). If patients are taking or have recently completed treatment with drugs listed in Table 1 within the prior 14 days, the dose adjustments are as shown in the table below [see Drug Interactions (7)].

Table 1. COLCRYS Dose Adjustment for Coadministration with Interacting Drugs if No Alternative Available [For magnitude of effect on colchicine plasma concentrations [see Clinical Pharmacology (12.3)]]
Strong CYP3A4 Inhibitors [Patients with renal or hepatic impairment should not be given COLCRYS in conjunction with strong CYP3A4 or P-gp inhibitors [see Contraindications (4)]]
Drug | Noted or Anticipated Outcome | Gout Flares |  |  |  | FMF
Drug | Noted or Anticipated Outcome | Prophylaxis of Gout Flares |  | Treatment of Gout Flares |  | FMF
Drug | Noted or Anticipated Outcome | Original Intended Dosage | Adjusted Dose | Original Intended Dosage | Adjusted Dose | Original Intended Dosage | Adjusted Dose
Atazanavir Clarithromycin Darunavir/Ritonavir [When used in combination with Ritonavir, see dosing recommendations for strong CYP3A4 inhibitors [see Contraindications (4)]] Indinavir Itraconazole Ketoconazole Lopinavir/Ritonavir Nefazodone Nelfinavir Ritonavir Saquinavir Telithromycin Tipranavir/Ritonavir | Significant increase in colchicine plasma levels; fatal colchicine toxicity has been reported with clarithromycin, a strong CYP3A4 inhibitor. Similarly, significant increase in colchicine plasma levels is anticipated with other strong CYP3A4 inhibitors. | 0.6 mg twice a day | 0.3 mg once a day | 1.2 mg (2 tablets) followed by 0.6 mg (1 tablet) 1 hour later. Dose to be repeated no earlier than 3 days. | 0.6 mg (1 tablet) × 1 dose, followed by 0.3 mg (1/2 tablet) 1 hour later. Dose to be repeated no earlier than 3 days. | Maximum daily dose of 1.2 – 2.4 mg | Maximum daily dose of 0.6 mg (may be given as 0.3 mg twice a day)
Atazanavir Clarithromycin Darunavir/Ritonavir [When used in combination with Ritonavir, see dosing recommendations for strong CYP3A4 inhibitors [see Contraindications (4)]] Indinavir Itraconazole Ketoconazole Lopinavir/Ritonavir Nefazodone Nelfinavir Ritonavir Saquinavir Telithromycin Tipranavir/Ritonavir | Significant increase in colchicine plasma levels; fatal colchicine toxicity has been reported with clarithromycin, a strong CYP3A4 inhibitor. Similarly, significant increase in colchicine plasma levels is anticipated with other strong CYP3A4 inhibitors. | 0.6 mg once a day | 0.3 mg once every other day | 1.2 mg (2 tablets) followed by 0.6 mg (1 tablet) 1 hour later. Dose to be repeated no earlier than 3 days. | 0.6 mg (1 tablet) × 1 dose, followed by 0.3 mg (1/2 tablet) 1 hour later. Dose to be repeated no earlier than 3 days. | Maximum daily dose of 1.2 – 2.4 mg | Maximum daily dose of 0.6 mg (may be given as 0.3 mg twice a day)
Moderate CYP3A4 Inhibitors
Drug | Noted or Anticipated Outcome | Gout Flares |  |  |  | FMF
Drug | Noted or Anticipated Outcome | Prophylaxis of Gout Flares |  | Treatment of Gout Flares |  | FMF
Drug | Noted or Anticipated Outcome | Original Intended Dosage | Adjusted Dose | Original Intended Dosage | Adjusted Dose | Original Intended Dosage | Adjusted Dose
Amprenavir Aprepitant Diltiazem Erythromycin Fluconazole Fosamprenavir (prodrug of Amprenavir) Grapefruit juice Verapamil | Significant increase in colchicine plasma concentration is anticipated. Neuromuscular toxicity has been reported with diltiazem and verapamil interactions. | 0.6 mg twice a day | 0.3 mg twice a day or 0.6 mg once a day | 1.2 mg (2 tablets) followed by 0.6 mg (1 tablet) 1 hour later. Dose to be repeated no earlier than 3 days. | 1.2 mg (2 tablets) × 1 dose. Dose to be repeated no earlier than 3 days. | Maximum daily dose of 1.2 – 2.4 mg | Maximum daily dose of 1.2 mg (may be given as 0.6 mg twice a day)
Amprenavir Aprepitant Diltiazem Erythromycin Fluconazole Fosamprenavir (prodrug of Amprenavir) Grapefruit juice Verapamil | Significant increase in colchicine plasma concentration is anticipated. Neuromuscular toxicity has been reported with diltiazem and verapamil interactions. | 0.6 mg once a day | 0.3 mg once a day | 1.2 mg (2 tablets) followed by 0.6 mg (1 tablet) 1 hour later. Dose to be repeated no earlier than 3 days. | 1.2 mg (2 tablets) × 1 dose. Dose to be repeated no earlier than 3 days. | Maximum daily dose of 1.2 – 2.4 mg | Maximum daily dose of 1.2 mg (may be given as 0.6 mg twice a day)
P-gp Inhibitors
Drug | Noted or Anticipated Outcome | Gout Flares |  |  |  | FMF
Drug | Noted or Anticipated Outcome | Prophylaxis of Gout Flares |  | Treatment of Gout Flares |  | FMF
Drug | Noted or Anticipated Outcome | Original Intended Dosage | Adjusted Dose | Original Intended Dosage | Adjusted Dose | Original Intended Dosage | Adjusted Dose
Cyclosporine Ranolazine | Significant increase in colchicine plasma levels; fatal colchicine toxicity has been reported with cyclosporine, a P-gp inhibitor. Similarly, significant increase in colchicine plasma levels is anticipated with other P-gp inhibitors. | 0.6 mg twice a day | 0.3 mg once a day | 1.2 mg (2 tablets) followed by 0.6 mg (1 tablet) 1 hour later. Dose to be repeated no earlier than 3 days. | 0.6 mg (1 tablet) × 1 dose. Dose to be repeated no earlier than 3 days. | Maximum daily dose of 1.2 – 2.4 mg | Maximum daily dose of 0.6 mg (may be given as 0.3 mg twice a day)
Cyclosporine Ranolazine | Significant increase in colchicine plasma levels; fatal colchicine toxicity has been reported with cyclosporine, a P-gp inhibitor. Similarly, significant increase in colchicine plasma levels is anticipated with other P-gp inhibitors. | 0.6 mg once a day | 0.3 mg once every other day | 1.2 mg (2 tablets) followed by 0.6 mg (1 tablet) 1 hour later. Dose to be repeated no earlier than 3 days. | 0.6 mg (1 tablet) × 1 dose. Dose to be repeated no earlier than 3 days. | Maximum daily dose of 1.2 – 2.4 mg | Maximum daily dose of 0.6 mg (may be given as 0.3 mg twice a day)

Table 2. COLCRYS Dose Adjustment for Coadministration with Protease Inhibitors
Protease Inhibitor | Clinical Comment | w/Colchicine - Prophylaxis of Gout Flares |  | w/Colchicine - Treatment of Gout Flares | w/Colchicine - Treatment of FMF
Atazanavir sulfate (Reyataz) | Patients with renal or hepatic impairment should not be given colchicine with Reyataz. | Original dose | Adjusted dose | 0.6 mg (1 tablet) × 1 dose, followed by 0.3 mg (1/2 tablet) 1 hour later. Dose to be repeated no earlier than 3 days. | Maximum daily dose of 0.6 mg (may be given as 0.3 mg twice a day)
Atazanavir sulfate (Reyataz) | Patients with renal or hepatic impairment should not be given colchicine with Reyataz. | 0.6 mg twice a day | 0.3 mg once a day | 0.6 mg (1 tablet) × 1 dose, followed by 0.3 mg (1/2 tablet) 1 hour later. Dose to be repeated no earlier than 3 days. | Maximum daily dose of 0.6 mg (may be given as 0.3 mg twice a day)
Atazanavir sulfate (Reyataz) | Patients with renal or hepatic impairment should not be given colchicine with Reyataz. | 0.6 mg once a day | 0.3 mg once every other day | 0.6 mg (1 tablet) × 1 dose, followed by 0.3 mg (1/2 tablet) 1 hour later. Dose to be repeated no earlier than 3 days. | Maximum daily dose of 0.6 mg (may be given as 0.3 mg twice a day)
Darunavir (Prezista) | Patients with renal or hepatic impairment should not be given colchicine with Prezista/ritonavir. | Original dose | Adjusted dose | 0.6 mg (1 tablet) × 1 dose, followed by 0.3 mg (1/2 tablet) 1 hour later. Dose to be repeated no earlier than 3 days. | Maximum daily dose of 0.6 mg (may be given as 0.3 mg twice a day)
Darunavir (Prezista) | Patients with renal or hepatic impairment should not be given colchicine with Prezista/ritonavir. | 0.6 mg twice a day | 0.3 mg once a day | 0.6 mg (1 tablet) × 1 dose, followed by 0.3 mg (1/2 tablet) 1 hour later. Dose to be repeated no earlier than 3 days. | Maximum daily dose of 0.6 mg (may be given as 0.3 mg twice a day)
Darunavir (Prezista) | Patients with renal or hepatic impairment should not be given colchicine with Prezista/ritonavir. | 0.6 mg once a day | 0.3 mg once every other day | 0.6 mg (1 tablet) × 1 dose, followed by 0.3 mg (1/2 tablet) 1 hour later. Dose to be repeated no earlier than 3 days. | Maximum daily dose of 0.6 mg (may be given as 0.3 mg twice a day)
Fosamprenavir (Lexiva) with Ritonavir | Patients with renal or hepatic impairment should not be given colchicine with Lexiva/ritonavir. | Original dose | Adjusted dose | 0.6 mg (1 tablet) × 1 dose, followed by 0.3 mg (1/2 tablet) 1 hour later. Dose to be repeated no earlier than 3 days. | Maximum daily dose of 0.6 mg (may be given as 0.3 mg twice a day)
Fosamprenavir (Lexiva) with Ritonavir | Patients with renal or hepatic impairment should not be given colchicine with Lexiva/ritonavir. | 0.6 mg twice a day | 0.3 mg once a day | 0.6 mg (1 tablet) × 1 dose, followed by 0.3 mg (1/2 tablet) 1 hour later. Dose to be repeated no earlier than 3 days. | Maximum daily dose of 0.6 mg (may be given as 0.3 mg twice a day)
Fosamprenavir (Lexiva) with Ritonavir | Patients with renal or hepatic impairment should not be given colchicine with Lexiva/ritonavir. | 0.6 mg once a day | 0.3 mg once every other day | 0.6 mg (1 tablet) × 1 dose, followed by 0.3 mg (1/2 tablet) 1 hour later. Dose to be repeated no earlier than 3 days. | Maximum daily dose of 0.6 mg (may be given as 0.3 mg twice a day)
Fosamprenavir (Lexiva) | Patients with renal or hepatic impairment should not be given colchicine with Lexiva/ritonavir. | Original dose | Adjusted dose | 1.2 mg (2 tablets) × 1 dose. Dose to be repeated no earlier than 3 days. | Maximum daily dose of 1.2 mg (may be given as 0.6 mg twice a day)
Fosamprenavir (Lexiva) | Patients with renal or hepatic impairment should not be given colchicine with Lexiva/ritonavir. | 0.6 mg twice a day | 0.3 mg twice a day or 0.6 mg once a day | 1.2 mg (2 tablets) × 1 dose. Dose to be repeated no earlier than 3 days. | Maximum daily dose of 1.2 mg (may be given as 0.6 mg twice a day)
Fosamprenavir (Lexiva) | Patients with renal or hepatic impairment should not be given colchicine with Lexiva/ritonavir. | 0.6 mg once a day | 0.3 mg once a day | 1.2 mg (2 tablets) × 1 dose. Dose to be repeated no earlier than 3 days. | Maximum daily dose of 1.2 mg (may be given as 0.6 mg twice a day)
Indinavir (Crixivan) | Patients with renal or hepatic impairment should not be given colchicine with Crixivan. | Original dose | Adjusted dose | 0.6 mg (1 tablet) × 1 dose, followed by 0.3 mg (1/2 tablet) 1 hour later. Dose to be repeated no earlier than 3 days. | Maximum daily dose of 0.6 mg (may be given as 0.3 mg twice a day)
Indinavir (Crixivan) | Patients with renal or hepatic impairment should not be given colchicine with Crixivan. | 0.6 mg twice a day | 0.3 mg once a day | 0.6 mg (1 tablet) × 1 dose, followed by 0.3 mg (1/2 tablet) 1 hour later. Dose to be repeated no earlier than 3 days. | Maximum daily dose of 0.6 mg (may be given as 0.3 mg twice a day)
Indinavir (Crixivan) | Patients with renal or hepatic impairment should not be given colchicine with Crixivan. | 0.6 mg once a day | 0.3 mg once every other day | 0.6 mg (1 tablet) × 1 dose, followed by 0.3 mg (1/2 tablet) 1 hour later. Dose to be repeated no earlier than 3 days. | Maximum daily dose of 0.6 mg (may be given as 0.3 mg twice a day)
Lopinavir/Ritonavir (Kaletra) | Patients with renal or hepatic impairment should not be given colchicine with Kaletra. | Original dose | Adjusted dose | 0.6 mg (1 tablet) × 1 dose, followed by 0.3 mg (1/2 tablet) 1 hour later. Dose to be repeated no earlier than 3 days. | Maximum daily dose of 0.6 mg (may be given as 0.3 mg twice a day)
Lopinavir/Ritonavir (Kaletra) | Patients with renal or hepatic impairment should not be given colchicine with Kaletra. | 0.6 mg twice a day | 0.3 mg once a day | 0.6 mg (1 tablet) × 1 dose, followed by 0.3 mg (1/2 tablet) 1 hour later. Dose to be repeated no earlier than 3 days. | Maximum daily dose of 0.6 mg (may be given as 0.3 mg twice a day)
Lopinavir/Ritonavir (Kaletra) | Patients with renal or hepatic impairment should not be given colchicine with Kaletra. | 0.6 mg once a day | 0.3 mg once every other day | 0.6 mg (1 tablet) × 1 dose, followed by 0.3 mg (1/2 tablet) 1 hour later. Dose to be repeated no earlier than 3 days. | Maximum daily dose of 0.6 mg (may be given as 0.3 mg twice a day)
Nelfinavir mesylate (Viracept) | Patients with renal or hepatic impairment should not be given colchicine with Viracept. | Original dose | Adjusted dose | 0.6 mg (1 tablet) × 1 dose, followed by 0.3 mg (1/2 tablet) 1 hour later. Dose to be repeated no earlier than 3 days. | Maximum daily dose of 0.6 mg (may be given as 0.3 mg twice a day)
Nelfinavir mesylate (Viracept) | Patients with renal or hepatic impairment should not be given colchicine with Viracept. | 0.6 mg twice a day | 0.3 mg once a day | 0.6 mg (1 tablet) × 1 dose, followed by 0.3 mg (1/2 tablet) 1 hour later. Dose to be repeated no earlier than 3 days. | Maximum daily dose of 0.6 mg (may be given as 0.3 mg twice a day)
Nelfinavir mesylate (Viracept) | Patients with renal or hepatic impairment should not be given colchicine with Viracept. | 0.6 mg once a day | 0.3 mg once every other day | 0.6 mg (1 tablet) × 1 dose, followed by 0.3 mg (1/2 tablet) 1 hour later. Dose to be repeated no earlier than 3 days. | Maximum daily dose of 0.6 mg (may be given as 0.3 mg twice a day)
Ritonavir (Norvir) | Patients with renal or hepatic impairment should not be given colchicine with Norvir. | Original dose | Adjusted dose | 0.6 mg (1 tablet) × 1 dose, followed by 0.3 mg (1/2 tablet) 1 hour later. Dose to be repeated no earlier than 3 days. | Maximum daily dose of 0.6 mg (may be given as 0.3 mg twice a day)
Ritonavir (Norvir) | Patients with renal or hepatic impairment should not be given colchicine with Norvir. | 0.6 mg twice a day | 0.3 mg once a day | 0.6 mg (1 tablet) × 1 dose, followed by 0.3 mg (1/2 tablet) 1 hour later. Dose to be repeated no earlier than 3 days. | Maximum daily dose of 0.6 mg (may be given as 0.3 mg twice a day)
Ritonavir (Norvir) | Patients with renal or hepatic impairment should not be given colchicine with Norvir. | 0.6 mg once a day | 0.3 mg once every other day | 0.6 mg (1 tablet) × 1 dose, followed by 0.3 mg (1/2 tablet) 1 hour later. Dose to be repeated no earlier than 3 days. | Maximum daily dose of 0.6 mg (may be given as 0.3 mg twice a day)
Saquinavir mesylate (Invirase) | Patients with renal or hepatic impairment should not be given colchicine with Invirase/ ritonavir. | Original dose | Adjusted dose | 0.6 mg (1 tablet) × 1 dose, followed by 0.3 mg (1/2 tablet) 1 hour later. Dose to be repeated no earlier than 3 days. | Maximum daily dose of 0.6 mg (may be given as 0.3 mg twice a day)
Saquinavir mesylate (Invirase) | Patients with renal or hepatic impairment should not be given colchicine with Invirase/ ritonavir. | 0.6 mg twice a day | 0.3 mg once a day | 0.6 mg (1 tablet) × 1 dose, followed by 0.3 mg (1/2 tablet) 1 hour later. Dose to be repeated no earlier than 3 days. | Maximum daily dose of 0.6 mg (may be given as 0.3 mg twice a day)
Saquinavir mesylate (Invirase) | Patients with renal or hepatic impairment should not be given colchicine with Invirase/ ritonavir. | 0.6 mg once a day | 0.3 mg once every other day | 0.6 mg (1 tablet) × 1 dose, followed by 0.3 mg (1/2 tablet) 1 hour later. Dose to be repeated no earlier than 3 days. | Maximum daily dose of 0.6 mg (may be given as 0.3 mg twice a day)
Tipranavir (Aptivus) | Patients with renal or hepatic impairment should not be given colchicine with Aptivus/ritonavir. | Original dose | Adjusted dose | 0.6 mg (1 tablet) × 1 dose, followed by 0.3 mg (1/2 tablet) 1 hour later. Dose to be repeated no earlier than 3 days. | Maximum daily dose of 0.6 mg (may be given as 0.3 mg twice a day)
Tipranavir (Aptivus) | Patients with renal or hepatic impairment should not be given colchicine with Aptivus/ritonavir. | 0.6 mg twice a day | 0.3 mg once a day | 0.6 mg (1 tablet) × 1 dose, followed by 0.3 mg (1/2 tablet) 1 hour later. Dose to be repeated no earlier than 3 days. | Maximum daily dose of 0.6 mg (may be given as 0.3 mg twice a day)
Tipranavir (Aptivus) | Patients with renal or hepatic impairment should not be given colchicine with Aptivus/ritonavir. | 0.6 mg once a day | 0.3 mg once every other day | 0.6 mg (1 tablet) × 1 dose, followed by 0.3 mg (1/2 tablet) 1 hour later. Dose to be repeated no earlier than 3 days. | Maximum daily dose of 0.6 mg (may be given as 0.3 mg twice a day)

Treatment of gout flares with COLCRYS is not recommended in patients receiving prophylactic dose of COLCRYS and CYP3A4 inhibitors.

2.5 Dose Modification in Renal Impairment

Colchicine dosing must be individualized according to the patient's renal function [see Use in Specific Populations (8.6)].

Clcr in mL/minute may be estimated from serum creatinine (mg/dL) determination using the following formula:

 | [140-age (years) × weight (kg)]
Clcr = | 72 × serum creatinine (mg/dL) × 0.85 for female patients

Gout Flares

Prophylaxis of Gout Flares

For prophylaxis of gout flares in patients with mild (estimated creatinine clearance [Clcr] 50 to 80 mL/min) to moderate (Clcr 30 to 50 mL/min) renal function impairment, adjustment of the recommended dose is not required, but patients should be monitored closely for adverse effects of colchicine. However, in patients with severe impairment, the starting dose should be 0.3 mg/day and any increase in dose should be done with close monitoring. For the prophylaxis of gout flares in patients undergoing dialysis, the starting doses should be 0.3 mg given twice a week with close monitoring [see Clinical Pharmacology (12.3), Use in Specific Populations (8.6)].

Treatment of Gout Flares

For treatment of gout flares in patients with mild (Clcr 50 to 80 mL/min) to moderate (Clcr 30 to 50 mL/min) renal function impairment, adjustment of the recommended dose is not required, but patients should be monitored closely for adverse effects of colchicine. However, in patients with severe impairment, while the dose does not need to be adjusted for the treatment of gout flares, a treatment course should be repeated no more than once every two weeks. For patients with gout flares requiring repeated courses, consideration should be given to alternate therapy. For patients undergoing dialysis, the total recommended dose for the treatment of gout flares should be reduced to a single dose of 0.6 mg (one tablet). For these patients, the treatment course should not be repeated more than once every two weeks [see Clinical Pharmacology (12.3), Use in Specific Populations (8.6)].

Treatment of gout flares with COLCRYS is not recommended in patients with renal impairment who are receiving COLCRYS for prophylaxis.

FMF

Caution should be taken in dosing patients with moderate and severe renal impairment and in patients undergoing dialysis. For these patients, the dosage should be reduced [see Clinical Pharmacology (12.3)]. Patients with mild (Clcr 50 to 80 mL/min) and moderate (Clcr 30 to 50 mL/min) renal impairment should be monitored closely for adverse effects of COLCRYS. Dose reduction may be necessary. For patients with severe renal failure (Clcr less than 30 mL/min), start with 0.3 mg/day; any increase in dose should be done with adequate monitoring of the patient for adverse effects of colchicine [see Use in Specific Populations (8.6)]. For patients undergoing dialysis, the total recommended starting dose should be 0.3 mg (half tablet) per day. Dosing can be increased with close monitoring. Any increase in dose should be done with adequate monitoring of the patient for adverse effects of colchicine [see Clinical Pharmacology (12.3), Use in Specific Populations (8.6)].

2.6 Dose Modification in Hepatic Impairment

Gout Flares

Prophylaxis of Gout Flares

For prophylaxis of gout flares in patients with mild to moderate hepatic function impairment, adjustment of the recommended dose is not required, but patients should be monitored closely for adverse effects of colchicine. Dose reduction should be considered for the prophylaxis of gout flares in patients with severe hepatic impairment [see Use in Specific Populations (8.7)].

Treatment of Gout Flares

For treatment of gout flares in patients with mild to moderate hepatic function impairment, adjustment of the recommended dose is not required, but patients should be monitored closely for adverse effects of colchicine. However, for the treatment of gout flares in patients with severe impairment, while the dose does not need to be adjusted, a treatment course should be repeated no more than once every two weeks. For these patients, requiring repeated courses for the treatment of gout flares, consideration should be given to alternate therapy [see Use in Specific Populations (8.7)].

Treatment of gout flares with COLCRYS is not recommended in patients with hepatic impairment who are receiving COLCRYS for prophylaxis.

FMF

Patients with mild to moderate hepatic impairment should be monitored closely for adverse effects of colchicine. Dose reduction should be considered in patients with severe hepatic impairment [see Use in Specific Populations (8.7)].

3 DOSAGE FORMS AND STRENGTHS

Tablets: 0.6 mg colchicine — purple capsule-shaped, film-coated with "AR 374" debossed on one side and scored on the other side.

4 CONTRAINDICATIONS

Patients with renal or hepatic impairment should not be given COLCRYS in conjunction with P-gp or strong CYP3A4 inhibitors (this includes all protease inhibitors except fosamprenavir). In these patients, life-threatening and fatal colchicine toxicity has been reported with colchicine taken in therapeutic doses.

5 WARNINGS AND PRECAUTIONS

5.1 Fatal Overdose

Fatal overdoses, both accidental and intentional, have been reported in adults and children who have ingested colchicine [see Overdosage (10)]. COLCRYS should be kept out of the reach of children.

5.2 Blood Dyscrasias

Myelosuppression, leukopenia, granulocytopenia, thrombocytopenia, pancytopenia and aplastic anemia have been reported with colchicine used in therapeutic doses.

5.3 Drug Interactions

Colchicine is a P-gp and CYP3A4 substrate. Life-threatening and fatal drug interactions have been reported in patients treated with colchicine given with P-gp and strong CYP3A4 inhibitors. If treatment with a P-gp or strong CYP3A4 inhibitor is required in patients with normal renal and hepatic function, the patient's dose of colchicine may need to be reduced or interrupted [see Drug Interactions (7)]. Use of COLCRYS in conjunction with P-gp or strong CYP3A4 inhibitors (this includes all protease inhibitors except fosamprenavir) is contraindicated in patients with renal or hepatic impairment [see Contraindications (4)].

5.4 Neuromuscular Toxicity

Colchicine-induced neuromuscular toxicity and rhabdomyolysis have been reported with chronic treatment in therapeutic doses. Patients with renal dysfunction and elderly patients, even those with normal renal and hepatic function, are at increased risk. Concomitant use of atorvastatin, simvastatin, pravastatin, fluvastatin, lovastatin, gemfibrozil, fenofibrate, fenofibric acid or benzafibrate (themselves associated with myotoxicity) or cyclosporine with COLCRYS may potentiate the development of myopathy [see Drug Interactions (7)]. Once colchicine is stopped, the symptoms generally resolve within one week to several months.

6 ADVERSE REACTIONS

Prophylaxis of Gout Flares

The most commonly reported adverse reaction in clinical trials of colchicine for the prophylaxis of gout was diarrhea.

Treatment of Gout Flares

The most common adverse reactions reported in the clinical trial with COLCRYS for treatment of gout flares were diarrhea (23%) and pharyngolaryngeal pain (3%).

FMF

Gastrointestinal tract adverse effects are the most frequent side effects in patients initiating COLCRYS, usually presenting within 24 hours, and occurring in up to 20% of patients given therapeutic doses. Typical symptoms include cramping, nausea, diarrhea, abdominal pain and vomiting. These events should be viewed as dose-limiting if severe, as they can herald the onset of more significant toxicity.

6.1 Clinical Trials Experience in Gout

Because clinical studies are conducted under widely varying and controlled conditions, adverse reaction rates observed in clinical studies of a drug cannot be directly compared to rates in the clinical studies of another drug and may not predict the rates observed in a broader patient population in clinical practice.

In a randomized, double-blind, placebo-controlled trial in patients with a gout flare, gastrointestinal adverse reactions occurred in 26% of patients using the recommended dose (1.8 mg over one hour) of COLCRYS compared to 77% of patients taking a nonrecommended high dose (4.8 mg over six hours) of colchicine and 20% of patients taking placebo. Diarrhea was the most commonly reported drug-related gastrointestinal adverse event. As shown in Table 3, diarrhea is associated with COLCRYS treatment. Diarrhea was more likely to occur in patients taking the high-dose regimen than the low-dose regimen. Severe diarrhea occurred in 19% and vomiting occurred in 17% of patients taking the nonrecommended high-dose colchicine regimen but did not occur in the recommended low-dose COLCRYS regimen.

Table 3. Number (%) of Patients with at Least One Drug-Related Treatment-Emergent Adverse Event with an Incidence of ≥2% of Patients in Any Treatment Group
MedDRA System Organ Class MedDRA Preferred Term | COLCRYS Dose |  | Placebo (N=59) n (%)
MedDRA System Organ Class MedDRA Preferred Term | High (N=52) n (%) | Low (N=74) n (%) | Placebo (N=59) n (%)
Number of Patients with at Least One Drug-Related TEAE | 40 (77) | 27 (37) | 16 (27)
Gastrointestinal Disorders | 40 (77) | 19 (26) | 12 (20)
Diarrhea | 40 (77) | 17 (23) | 8 (14)
Nausea | 9 (17) | 3 (4) | 3 (5)
Vomiting | 9 (17) | 0 | 0
Abdominal Discomfort | 0 | 0 | 2 (3)
General Disorders and Administration Site Conditions | 4 (8) | 1 (1) | 1 (2)
Fatigue | 2 (4) | 1 (1) | 1 (2)
Metabolic and Nutrition Disorders | 0 | 3 (4) | 2 (3)
Gout | 0 | 3 (4) | 1 (2)
Nervous System Disorders | 1 (2) | 1 (1.4) | 2 (3)
Headache | 1 (2) | 1 (1) | 2 (3)
Respiratory Thoracic Mediastinal Disorders | 1 (2) | 2 (3) | 0
Pharyngolaryngeal Pain | 1 (2) | 2 (3) | 0

6.2 Postmarketing Experience

Serious toxic manifestations associated with colchicine include myelosuppression, disseminated intravascular coagulation and injury to cells in the renal, hepatic, circulatory and central nervous systems.

These most often occur with excessive accumulation or overdosage [see Overdosage (10)].

The following adverse reactions have been identified with colchicine. These have been generally reversible upon temporarily interrupting treatment or lowering the dose of colchicine. Because these reactions are reported voluntarily from a population of uncertain size, it is not always possible to reliably estimate their frequency or establish a causal relationship to drug exposure.

Neurological: sensory motor neuropathy

Dermatological: alopecia, maculopapular rash, purpura, rash

Digestive: abdominal cramping, abdominal pain, diarrhea, lactose intolerance, nausea, vomiting

Hematological: leukopenia, granulocytopenia, thrombocytopenia, pancytopenia, aplastic anemia

Hepatobiliary: elevated AST, elevated ALT

Musculoskeletal: myopathy, elevated CPK, myotonia, muscle weakness, muscle pain, rhabdomyolysis

Reproductive: azoospermia, oligospermia

7 DRUG INTERACTIONS

COLCRYS (colchicine) is a substrate of the efflux transporter P-glycoprotein (P-gp). Of the cytochrome P450 enzymes tested, CYP3A4 was mainly involved in the metabolism of colchicine. If COLCRYS is administered with drugs that inhibit P-gp, most of which also inhibit CYP3A4, increased concentrations of colchicine are likely. Fatal drug interactions have been reported.

Physicians should ensure that patients are suitable candidates for treatment with COLCRYS and remain alert for signs and symptoms of toxicities related to increased colchicine exposure as a result of a drug interaction. Signs and symptoms of COLCRYS toxicity should be evaluated promptly and, if toxicity is suspected, COLCRYS should be discontinued immediately.

Table 4 provides recommendations as a result of other potentially significant drug interactions. Table 1 provides recommendations for strong and moderate CYP3A4 inhibitors and P-gp inhibitors.

Table 4. Other Potentially Significant Drug Interactions
Concomitant Drug Class or Food | Noted or Anticipated Outcome | Clinical Comment
HMG-Co A Reductase Inhibitors: atorvastatin, fluvastatin, lovastatin, pravastatin, simvastatin | Pharmacokinetic and/or pharmacodynamic interaction: the addition of one drug to a stable long-term regimen of the other has resulted in myopathy and rhabdomyolysis (including a fatality) | Weigh the potential benefits and risks and carefully monitor patients for any signs or symptoms of muscle pain, tenderness, or weakness, particularly during initial therapy; monitoring CPK (creatine phosphokinase) will not necessarily prevent the occurrence of severe myopathy.
Other Lipid-Lowering Drugs: fibrates, gemfibrozil | Pharmacokinetic and/or pharmacodynamic interaction: the addition of one drug to a stable long-term regimen of the other has resulted in myopathy and rhabdomyolysis (including a fatality) | Weigh the potential benefits and risks and carefully monitor patients for any signs or symptoms of muscle pain, tenderness, or weakness, particularly during initial therapy; monitoring CPK (creatine phosphokinase) will not necessarily prevent the occurrence of severe myopathy.
Digitalis Glycosides: digoxin | P-gp substrate; rhabdomyolysis has been reported | Weigh the potential benefits and risks and carefully monitor patients for any signs or symptoms of muscle pain, tenderness, or weakness, particularly during initial therapy; monitoring CPK (creatine phosphokinase) will not necessarily prevent the occurrence of severe myopathy.

8 USE IN SPECIFIC POPULATIONS

8.1 Pregnancy

Risk Summary

Available data from published literature on colchicine use in pregnancy over several decades have not identified any drug associated risks for major birth defects, miscarriage, or adverse maternal or fetal outcomes (see Data). Colchicine crosses the human placenta. Although animal reproductive and developmental studies were not conducted with COLCRYS (colchicine), published animal reproduction and development studies indicate that colchicine causes embryofetal toxicity, teratogenicity and altered postnatal development at exposures within or above the clinical therapeutic range.

The estimated background risk of major birth defects and miscarriage for the indicated population is unknown. All pregnancies have a background risk of birth defect, loss, or other adverse outcomes. In the U.S. general population, the estimated background risk of major birth defects and miscarriage in clinically recognized pregnancies is 2 to 4% and 15 to 20%, respectively.

Data

Human Data

Available data from published observational studies, case series, and case reports over several decades do not suggest an increased risk for major birth defects or miscarriage in pregnant women with rheumatic diseases (such as rheumatoid arthritis, Behcet's disease, or familial Mediterranean fever (FMF) treated with colchicine at therapeutic doses during pregnancy. Limitations of these data include the lack of randomization and inability to control for confounders such as underlying maternal disease and maternal use of concomitant medications.

8.2 Lactation

Risk Summary

Colchicine is present in human milk (see Data). Adverse events in breastfed infants have not been reported in the published literature after administration of colchicine to lactating women. There are no data on the effects of colchicine on milk production. The developmental and health benefits of breastfeeding should be considered along with the mother's clinical need for COLCRYS and any potential adverse effects on the breastfed child from COLCRYS or from the underlying maternal condition.

Data

Limited published data from case reports and a small lactation study demonstrate that colchicine is present in breastmilk. A systematic review of literature reported no adverse effects in 149 breastfed children. In a prospective observational cohort study, no gastrointestinal or other symptoms were reported in 38 colchicine-exposed breastfed infants.

8.3 Females and Males of Reproductive Potential

Infertility

Case reports and epidemiology studies in human male subjects on colchicine therapy indicated that infertility from colchicine is rare and may be reversible. A case report indicated that azoospermia was reversed when therapy was stopped. Case reports and epidemiology studies in female subjects on colchicine therapy have not established a clear relationship between colchicine use and female infertility. However, since the progression of FMF without treatment may result in infertility, the use of colchicine needs to be weighed against the potential risks [see Nonclinical Toxicology (13.1)].

8.4 Pediatric Use

The safety and efficacy of colchicine in children of all ages with FMF has been evaluated in uncontrolled studies. There does not appear to be an adverse effect on growth in children with FMF treated long-term with colchicine.

Safety and effectiveness of colchicine in pediatric patients with gout has not been established.

8.5 Geriatric Use

Clinical studies with colchicine for prophylaxis and treatment of gout flares and for treatment of FMF did not include sufficient numbers of patients aged 65 years and older to determine whether they respond differently from younger patients. In general, dose selection for an elderly patient with gout should be cautious, reflecting the greater frequency of decreased renal function, concomitant disease or other drug therapy [see Dosage and Administration (2.4), Clinical Pharmacology (12.3)].

8.6 Renal Impairment

Colchicine is significantly excreted in urine in healthy subjects. Clearance of colchicine is decreased in patients with impaired renal function. Total body clearance of colchicine was reduced by 75% in patients with end-stage renal disease undergoing dialysis.

Prophylaxis of Gout Flares

For prophylaxis of gout flares in patients with mild (estimated creatinine clearance Clcr 50 to 80 mL/min) to moderate (Clcr 30 to 50 mL/min) renal function impairment, adjustment of the recommended dose is not required, but patients should be monitored closely for adverse effects of colchicine. However, in patients with severe impairment, the starting dose should be 0.3 mg per day and any increase in dose should be done with close monitoring. For the prophylaxis of gout flares in patients undergoing dialysis, the starting doses should be 0.3 mg given twice a week with close monitoring [see Dosage and Administration (2.5)].

Treatment of Gout Flares

For treatment of gout flares in patients with mild (Clcr 50 to 80 mL/min) to moderate (Clcr 30 to 50 mL/min) renal function impairment, adjustment of the recommended dose is not required, but patients should be monitored closely for adverse effects of COLCRYS. However, in patients with severe impairment, while the dose does not need to be adjusted for the treatment of gout flares, a treatment course should be repeated no more than once every two weeks. For patients with gout flares requiring repeated courses, consideration should be given to alternate therapy. For patients undergoing dialysis, the total recommended dose for the treatment of gout flares should be reduced to a single dose of 0.6 mg (one tablet). For these patients, the treatment course should not be repeated more than once every two weeks [see Dosage and Administration (2.5)].

FMF

Although pharmacokinetics of colchicine in patients with mild (Clcr 50 to 80 mL/min) and moderate (Clcr 30 to 50 mL/min) renal impairment is not known, these patients should be monitored closely for adverse effects of colchicine. Dose reduction may be necessary. In patients with severe renal failure (Clcr less than 30 mL/min) and end-stage renal disease requiring dialysis, COLCRYS may be started at the dose of 0.3 mg/day. Any increase in dose should be done with adequate monitoring of the patient for adverse effects of COLCRYS [see Clinical Pharmacology (12.3), Dosage and Administration (2.5)].

8.7 Hepatic Impairment

The clearance of colchicine may be significantly reduced and plasma half-life prolonged in patients with chronic hepatic impairment compared to healthy subjects [see Clinical Pharmacology (12.3)].

Prophylaxis of Gout Flares

For prophylaxis of gout flares in patients with mild to moderate hepatic function impairment, adjustment of the recommended dose is not required, but patients should be monitored closely for adverse effects of colchicine. Dose reduction should be considered for the prophylaxis of gout flares in patients with severe hepatic impairment [see Dosage and Administration (2.6)].

Treatment of Gout Flares

For treatment of gout flares in patients with mild to moderate hepatic function impairment, adjustment of the recommended COLCRYS dose is not required, but patients should be monitored closely for adverse effects of COLCRYS. However, for the treatment of gout flares in patients with severe impairment, while the dose does not need to be adjusted, the treatment course should be repeated no more than once every two weeks. For these patients, requiring repeated courses for the treatment of gout flares, consideration should be given to alternate therapy [see Dosage and Administration (2.6)].

FMF

In patients with severe hepatic disease, dose reduction should be considered with careful monitoring [see Clinical Pharmacology (12.3), Dosage and Administration (2.6)].

9 DRUG ABUSE AND DEPENDENCE

Tolerance, abuse or dependence with colchicine has not been reported.

10 OVERDOSAGE

The exact dose of colchicine that produces significant toxicity is unknown. Fatalities have occurred after ingestion of a dose as low as 7 mg over a four day period, while other patients have survived after ingesting more than 60 mg. A review of 150 patients who overdosed on colchicine found that those who ingested less than 0.5 mg/kg survived and tended to have milder toxicities such as gastrointestinal symptoms, whereas those who took 0.5 to 0.8 mg/kg had more severe reactions such as myelosuppression. There was 100% mortality in those who ingested more than 0.8 mg/kg.

The first stage of acute colchicine toxicity typically begins within 24 hours of ingestion and includes gastrointestinal symptoms such as abdominal pain, nausea, vomiting, diarrhea and significant fluid loss, leading to volume depletion. Peripheral leukocytosis may also be seen. Life-threatening complications occur during the second stage, which occurs 24 to 72 hours after drug administration, attributed to multiorgan failure and its consequences. Death is usually a result of respiratory depression and cardiovascular collapse. If the patient survives, recovery of multiorgan injury may be accompanied by rebound leukocytosis and alopecia starting about one week after the initial ingestion.

Treatment of colchicine poisoning should begin with gastric lavage and measures to prevent shock. Otherwise, treatment is symptomatic and supportive. No specific antidote is known. Colchicine is not effectively removed by dialysis [see Clinical Pharmacology (12.3)].

11 DESCRIPTION

Colchicine is an alkaloid chemically described as (S)N- (5,6,7,9-tetrahydro- 1,2,3, 10-tetramethoxy-9-oxobenzo [alpha] heptalen-7-yl) acetamide with a molecular formula of C22H25NO6 and a molecular weight of 399.4. The structural formula of colchicine is given below.

Colchicine occurs as a pale yellow powder that is soluble in water.

COLCRYS (colchicine, USP) tablets are supplied for oral administration as purple, film-coated, capsule-shaped tablets (0.1575" × 0.3030"), debossed with "AR 374" on one side and scored on the other, containing 0.6 mg of the active ingredient colchicine USP. Inactive ingredients: carnauba wax, FD&C blue #2, FD&C red #40, hypromellose, lactose monohydrate, magnesium stearate, microcrystalline cellulose, polydextrose, polyethylene glycol, pregelatinized starch, sodium starch glycolate, titanium dioxide and triacetin.

12 CLINICAL PHARMACOLOGY

12.1 Mechanism of Action

The mechanism by which COLCRYS exerts its beneficial effect in patients with FMF has not been fully elucidated; however, evidence suggests that colchicine may interfere with the intracellular assembly of the inflammasome complex present in neutrophils and monocytes that mediates activation of interleukin-1β. Additionally, colchicine disrupts cytoskeletal functions through inhibition of β-tubulin polymerization into microtubules and consequently prevents the activation, degranulation and migration of neutrophils thought to mediate some gout symptoms.

12.3 Pharmacokinetics

Absorption

In healthy adults, COLCRYS is absorbed when given orally, reaching a mean Cmax of 2.5 ng/mL (range 1.1 to 4.4 ng/mL) in one to two hours (range 0.5 to 3 hours) after a single dose administered under fasting conditions.

Following oral administration of COLCRYS given as 1.8 mg colchicine over one hour to healthy, young adults under fasting conditions, colchicine appears to be readily absorbed, reaching mean maximum plasma concentrations of 6.2 ng/mL at a median 1.81 hours (range: 1.0 to 2.5 hours). Following administration of the nonrecommended high-dose regimen (4.8 mg over six hours), mean maximal plasma concentrations were 6.8 ng/mL, at a median 4.47 hours (range: 3.1 to 7.5 hours).

After ten days on a regimen of 0.6 mg twice daily, peak concentrations are 3.1 to 3.6 ng/mL (range 1.6 to 6.0 ng/mL), occurring 1.3 to 1.4 hours postdose (range 0.5 to 3.0 hours). Mean pharmacokinetic parameter values in healthy adults are shown in Table 5.

Table 5. Mean (%CV) Pharmacokinetic Parameters in Healthy Adults Given COLCRYS
Cmax (Colchicine ng/mL) | Tmax [Tmax mean (range)] (h) | Vd/F (L) | CL/F (L/hr) | t1/2 (h)
COLCRYS 0.6 mg Single Dose (N=13)
2.5 (28.7) | 1.5 (1.0 – 3.0) | 341.5 (54.4) | 54.1 (31.0) | --
COLCRYS 0.6 mg Twice Daily × 10 Days (N=13)
3.6 (23.7) | 1.3 (0.5 – 3.0) | 1150 (18.7) | 30.3 (19.0) | 26.6 (16.3)
CL = Dose/AUC0-t (calculated from mean values)
Vd = CL/Ke (calculated from mean values)

In some subjects, secondary colchicine peaks are seen, occurring between three and 36 hours postdose and ranging from 39 to 155% of the height of the initial peak. These observations are attributed to intestinal secretion and reabsorption and/or biliary recirculation.

Absolute bioavailability is reported to be approximately 45%.

Administration of COLCRYS with food has no effect on the rate of colchicine absorption but does decrease the extent of colchicine by approximately 15%. This is without clinical significance.

Distribution

The mean apparent volume of distribution in healthy young volunteers is approximately 5 to 8 L/kg.

Colchicine binding to serum protein is low, 39 ± 5%, primarily to albumin regardless of concentration.

Colchicine crosses the placenta (plasma levels in the fetus are reported to be approximately 15% of the maternal concentration). Colchicine also distributes into breast milk at concentrations similar to those found in the maternal serum [see Use in Specific Populations (8.1, 8.2)].

Metabolism

Colchicine is demethylated to two primary metabolites, 2-O-demethylcolchicine and 3-O-demethylcolchicine (2- and 3-DMC, respectively) and one minor metabolite, 10-O-demethylcolchicine (also known as colchiceine). In vitro studies using human liver microsomes have shown that CYP3A4 is involved in the metabolism of colchicine to 2- and 3-DMC. Plasma levels of these metabolites are minimal (less than 5% of parent drug).

Elimination/Excretion

In healthy volunteers (n=12), 40 to 65% of 1 mg orally administered colchicine was recovered unchanged in urine. Enterohepatic recirculation and biliary excretion are also postulated to play a role in colchicine elimination. Following multiple oral doses (0.6 mg twice daily), the mean elimination half-lives in young healthy volunteers (mean age 25 to 28 years of age) is 26.6 to 31.2 hours. Colchicine is a substrate of P-gp.

Extracorporeal Elimination

Colchicine is not removed by hemodialysis.

Special Populations

There is no difference between men and women in the pharmacokinetic disposition of colchicine.

Pediatric Patients

Pharmacokinetics of colchicine was not evaluated in pediatric patients.

Elderly

A published report described the pharmacokinetics of 1 mg oral colchicine tablet in four elderly women compared to six young healthy males. The mean age of the four elderly women was 83 years (range 75 to 93), mean weight was 47 kg (38 to 61 kg) and mean creatinine clearance was 46 mL/min (range 25 to 75 mL/min). Mean peak plasma levels and AUC of colchicine were two times higher in elderly subjects compared to young healthy males.

A pharmacokinetic study using a single oral dose of one 0.6 mg colchicine tablet was conducted in young healthy subjects (n=20) between the ages of 18 and 30 years and elderly subjects (n=18) between the ages of 60 and 70 years. Elderly subjects in this study had a median age of 62 years and a mean (±SD) age of 62.83 ± 2.83 years. A statistically significant difference in creatinine clearance (mean ± SD) was found between the two age groups (132.56 ± 23.16 mL/min for young vs 87.02 ± 17.92 mL/min for elderly subjects, respectively). The following pharmacokinetic parameter values (mean ± SD) were observed for colchicine in the young and elderly subjects, respectively: AUC0-inf (ng/hr/mL) 22.39 ± 6.95 and 25.01 ± 6.92; Cmax (ng/mL) 2.61 ± 0.71 and 2.56 ± 0.97; Tmax (hr) 1.38 ± 0.42 and 1.25 ± 0.43; apparent elimination half-life (hr) 24.92 ± 5.34 and 30.06 ± 10.78; and clearance (mL/min) 0.0321 ± 0.0091 and 0.0292 ± 0.0071.

Clinical studies with colchicine for prophylaxis and treatment of gout flares and for treatment of FMF did not include sufficient numbers of patients aged 65 years and older to determine whether they respond differently than younger patients. In general, dose selection for an elderly patient with gout should be cautious, reflecting the greater frequency of decreased renal function, concomitant disease or other drug therapy [see Dosage and Administration (2.4), Use in Specific Populations (8.5)].

Renal Impairment

Pharmacokinetics of colchicine in patients with mild and moderate renal impairment is not known. A published report described the disposition of colchicine (1 mg) in young adult men and women with FMF who had normal renal function or end-stage renal disease requiring dialysis. Patients with end-stage renal disease had 75% lower colchicine clearance (0.17 vs 0.73 L/hr/kg) and prolonged plasma elimination half-life (18.8 vs 4.4 hours) as compared to subjects with FMF and normal renal function [see Dosage and Administration (2.5), Use in Specific Populations (8.6)].

Hepatic Impairment

Published reports on the pharmacokinetics of IV colchicine in patients with severe chronic liver disease, as well as those with alcoholic or primary biliary cirrhosis and normal renal function suggest wide interpatient variability. In some subjects with mild to moderate cirrhosis, the clearance of colchicine is significantly reduced and plasma half-life prolonged compared to healthy subjects. In subjects with primary biliary cirrhosis, no consistent trends were noted [see Dosage and Administration (2.6), Use in Specific Populations (8.7)]. No pharmacokinetic data are available for patients with severe hepatic impairment (Child-Pugh C).

Drug Interactions

In Vitro Drug Interactions

In vitro studies in human liver microsomes have shown that colchicine is not an inhibitor or inducer of CYP1A2, CYP2A6, CYP2B6, CYP2C8, CYP2C9, CYP2C19, CYP2D6, CYP2E1 or CYP3A4 activity.

In Vivo Drug Interactions

The effects of coadministration of other drugs with COLCRYS on Cmax, AUC and Cmin are summarized in Table 6 (effect of other drugs on colchicine) and Table 7 (effect of colchicine on other drugs). For information regarding clinical recommendations, see Table 1 in Dose Modification for Coadministration of Interacting Drugs [see Dosage and Administration (2.4)].

Table 6. Drug Interactions: Pharmacokinetic Parameters for COLCRYS (Colchicine, USP) Tablets in the Presence of the Coadministered Drug
Coadministered Drug | Dose of Coadministered Drug (mg) | Dose of COLCRYS (mg) | N | % Change in Colchicine Concentrations from Baseline (Range: Min - Max)
Coadministered Drug | Dose of Coadministered Drug (mg) | Dose of COLCRYS (mg) | N | Cmax | AUC0-t
Cyclosporine | 100 mg single dose | 0.6 mg single dose | 23 | 270.0 (62.0 to 606.9) | 259.0 (75.8 to 511.9)
Clarithromycin | 250 mg twice daily, 7 days | 0.6 mg single dose | 23 | 227.2 (65.7 to 591.1) | 281.5 (88.7 to 851.6)
Ketoconazole | 200 mg twice daily, 5 days | 0.6 mg single dose | 24 | 101.7 (19.6 to 219.0) | 212.2 (76.7 to 419.6)
Ritonavir | 100 mg twice daily, 5 days | 0.6 mg single dose | 18 | 184.4 (79.2 to 447.4) | 296.0 (53.8 to 924.4)
Verapamil | 240 mg daily, 5 days | 0.6 mg single dose | 24 | 40.1 (-47.1 to 149.5) | 103.3 (-9.8 to 217.2)
Diltiazem | 240 mg daily, 7 days | 0.6 mg single dose | 20 | 44.2 (-46.0 to 318.3) | 93.4 (-30.2 to 338.6)
Azithromycin | 500 mg × 1 day, then 250 mg × 4 days | 0.6 mg single dose | 21 | 21.6 (-41.7 to 222.0) | 57.1 (-24.3 to 241.1)
Grapefruit juice | 240 mL twice daily, 4 days | 0.6 mg single dose | 21 | -2.55 (-53.4 to 55.0) | -2.36 (-46.4 to 62.2)

Estrogen-containing oral contraceptives: In healthy female volunteers given ethinyl estradiol and norethindrone (Ortho-Novum 1/35) coadministered with COLCRYS (0.6 mg twice daily × 14 days), hormone concentrations are not affected.

In healthy volunteers given theophylline coadministered with COLCRYS (0.6 mg twice daily × 14 days), theophylline concentrations were not affected.

Table 7. Drug Interactions: Pharmacokinetic Parameters for Coadministration of Drug in the Presence of COLCRYS (Colchicine, USP) Tablets
Coadministered Drug | Dose of Coadministered Drug (mg) | Dose of COLCRYS (mg) | N | % Change in Coadministered Drug Concentrations from Baseline (Range: Min - Max)
Coadministered Drug | Dose of Coadministered Drug (mg) | Dose of COLCRYS (mg) | N | Cmax | AUC0-t
Theophylline | 300 mg (elixir) single dose | 0.6 mg twice daily × 14 days | 27 | 1.6 (-30.4 to 23.1) | 1.6 (-28.5 to 27.1)
Ethinyl Estradiol (Ortho-Novum 1/35) | 21 day cycle (active treatment) + 7 day placebo | 0.6 mg twice daily × 14 days | 27 [Conducted in healthy adult females] | -6.7 (-40.3 to 44.7) | -3.0 [AUCτ] (-25.3 to 24.9)
Norethindrone (Ortho-Novum 1/35) | 21 day cycle (active treatment) + 7 day placebo | 0.6 mg twice daily × 14 days | 27 [Conducted in healthy adult females] | 0.94 (-37.3 to 59.4) | -1.6 (-32.0 to 33.7)

13 NONCLINICAL TOXICOLOGY

13.1 Carcinogenesis, Mutagenesis, Impairment of Fertility

Carcinogenesis

Two year studies were conducted in mice and rats to assess the carcinogenic potential of colchicine. No evidence of colchicine-related tumorigenicity was observed in mice or rats at colchicine oral doses up to 3 and 2 mg/kg/day, respectively (approximately six and eight times, respectively, the maximum recommended human dose of 2.4 mg on a mg/m^2 basis).

Mutagenesis

Colchicine was negative for mutagenicity in the bacterial reverse mutation assay. In a chromosomal aberration assay in cultured human white blood cells, colchicine treatment resulted in the formation of micronuclei. Since published studies demonstrated that colchicine induces aneuploidy from the process of mitotic nondisjunction without structural DNA changes, colchicine is not considered clastogenic, although micronuclei are formed.

Impairment of Fertility

No studies of colchicine effects on fertility were conducted with COLCRYS. However, published nonclinical studies demonstrated that colchicine-induced disruption of microtubule formation affects meiosis and mitosis. Reproductive studies also reported abnormal sperm morphology and reduced sperm counts in males, and interference with sperm penetration, second meiotic division and normal cleavage in females when exposed to colchicine. Colchicine administered to pregnant animals resulted in fetal death and teratogenicity. These effects were dose-dependent, with the timing of exposure critical for the effects on embryofetal development. The nonclinical doses evaluated were generally higher than an equivalent human therapeutic dose, but safety margins for reproductive and developmental toxicity could not be determined.

14 CLINICAL STUDIES

The evidence for the efficacy of colchicine in patients with chronic gout is derived from the published literature. Two randomized clinical trials assessed the efficacy of colchicine 0.6 mg twice a day for the prophylaxis of gout flares in patients with gout initiating treatment with urate-lowering therapy. In both trials, treatment with colchicine decreased the frequency of gout flares.

The efficacy of a low-dosage regimen of oral colchicine (COLCRYS total dose 1.8 mg over one hour) for treatment of gout flares was assessed in a multicenter, randomized, double-blind, placebo-controlled, parallel group, one week, dose-comparison study. Patients meeting American College of Rheumatology criteria for gout were randomly assigned to three groups: high-dose colchicine (1.2 mg, then 0.6 mg hourly × 6 hours [4.8 mg total]); low-dose colchicine (1.2 mg, then 0.6 mg in one hour [1.8 mg total] followed by five placebo doses hourly); or placebo (two capsules, then one capsule hourly × six hours). Patients took the first dose within 12 hours of the onset of the flare and recorded pain intensity (11-point Likert scale) and adverse events over 72 hours. The efficacy of colchicine was measured based on response to treatment in the target joint, using patient self-assessment of pain at 24 hours following the time of first dose as recorded in the diary. A responder was one who achieved at least a 50% reduction in pain score at the 24-hour postdose assessment relative to the pretreatment score and did not use rescue medication prior to the actual time of 24-hour postdose assessment.

Rates of response were similar for the recommended low-dose treatment group (38%) and the nonrecommended high-dose group (33%) but were higher as compared to the placebo group (16%) as shown in Table 8.

Table 8. Number (%) of Responders Based on Target Joint Pain Score at 24 Hours Post First Dose
COLCRYS Dose Responders n (%) |  |  | % Differences in Proportion
Low-Dose (n=74) | High-Dose (n=52) | Placebo n (%) (n=58) | Low-Dose vs Placebo (95% CI) | High-Dose vs Placebo (95% CI)
28 (38%) | 17 (33%) | 9 (16%) | 22 (8, 37) | 17 (1, 33)

Figure 1 shows the percentage of patients achieving varying degrees of improvement in pain from baseline at 24 hours.

Figure 1
Pain Relief on Low and High Doses of COLCRYS and Placebo (Cumulative)

The evidence for the efficacy of colchicine in patients with FMF is derived from the published literature. Three randomized, placebo-controlled studies were identified. The three placebo-controlled studies randomized a total of 48 adult patients diagnosed with FMF and reported similar efficacy endpoints as well as inclusion and exclusion criteria.

One of the studies randomized 15 patients with FMF to a six month crossover study during which five patients discontinued due to study noncompliance. The ten patients completing the study experienced five attacks over the course of 90 days while treated with colchicine compared to 59 attacks over the course of 90 days while treated with placebo. Similarly, the second study randomized 22 patients with FMF to a four month crossover study during which nine patients discontinued due to lack of efficacy while receiving placebo or study noncompliance. The 13 patients completing the study experienced 18 attacks over the course of 60 days while treated with colchicine compared to 68 attacks over the course of 60 days while treated with placebo. The third study was discontinued after an interim analysis of six of the 11 patients enrolled had completed the study; results could not be confirmed.

Open-label experience with colchicine in adults and children with FMF is consistent with the randomized, controlled trial experience and was utilized to support information on the safety profile of colchicine and for dosing recommendations.

16 HOW SUPPLIED/STORAGE AND HANDLING

16.1 How Supplied

COLCRYS (colchicine, USP) tablets 0.6 mg are purple, film-coated, capsule-shaped tablets debossed with "AR 374" on one side and scored on the other side.

Bottles of 30 | NDC 64764-119-07
Bottles of 60 | NDC 64764-119-06
Bottles of 100 | NDC 64764-119-01
Bottles of 1000 | NDC 64764-119-10

16.2 Storage

Store at 20°C to 25°C (68°F to 77°F) [See USP Controlled Room Temperature].

Protect from light.

DISPENSE IN TIGHT, LIGHT-RESISTANT CONTAINER.

17 PATIENT COUNSELING INFORMATION

Advise the patient to read the FDA-approved patient labeling (Medication Guide).

Dosing Instructions

Patients should be advised to take COLCRYS as prescribed, even if they are feeling better. Patients should not alter the dose or discontinue treatment without consulting with their doctor. If a dose of COLCRYS is missed:

- For treatment of a gout flare when the patient is not being dosed for prophylaxis, take the missed dose as soon as possible.
- For treatment of a gout flare during prophylaxis, take the missed dose immediately, wait 12 hours, then resume the previous dosing schedule.
- For prophylaxis without treatment for a gout flare, or FMF, take the dose as soon as possible and then return to the normal dosing schedule. However, if a dose is skipped the patient should not double the next dose.

Fatal Overdose

Instruct patient that fatal overdoses, both accidental and intentional, have been reported in adults and children who have ingested colchicine. COLCRYS should be kept out of the reach of children.

Blood Dyscrasias

Patients should be informed that bone marrow depression with agranulocytosis, aplastic anemia and thrombocytopenia may occur with COLCRYS.

Drug and Food Interactions

Patients should be advised that many drugs or other substances may interact with COLCRYS and some interactions could be fatal. Therefore, patients should report to their healthcare provider all of the current medications they are taking and check with their healthcare provider before starting any new medications, particularly antibiotics. Patients should also be advised to report the use of nonprescription medication or herbal products. Grapefruit and grapefruit juice may also interact and should not be consumed during COLCRYS treatment.

Neuromuscular Toxicity

Patients should be informed that muscle pain or weakness, tingling or numbness in fingers or toes may occur with COLCRYS alone or when it is used with certain other drugs. Patients developing any of these signs or symptoms must discontinue COLCRYS and seek medical evaluation immediately.

Infertility

Advise males of reproductive potential that COLCRYS may rarely and transiently impair fertility [see Use in Specific Populations (8.3)].

MEDICATION GUIDE
COLCRYS (KOL-kris)
(colchicine)
tablets, for oral use

Read the Medication Guide that comes with COLCRYS before you start taking it and each time you get a refill. There may be new information. This Medication Guide does not take the place of talking to your healthcare provider about your medical condition or treatment. You and your healthcare provider should talk about COLCRYS when you start taking it and at regular checkups.

What is the most important information that I should know about COLCRYS?

COLCRYS can cause serious side effects or death if levels of COLCRYS are too high in your body.

- Taking certain medicines with COLCRYS can cause your level of COLCRYS to be too high, especially if you have kidney or liver problems.
- Tell your healthcare provider about all your medical conditions, including if you have kidney or liver problems. Your dose of COLCRYS may need to be changed.
- Tell your healthcare provider about all the medicines you take, including prescription and nonprescription medicines, vitamins and herbal supplements.
- Even medicines that you take for a short period of time, such as antibiotics, can interact with COLCRYS and cause serious side effects or death.
- Talk to your healthcare provider or pharmacist before taking any new medicine.
- Especially tell your healthcare provider if you take:

- atazanavir sulfate (Reyataz)
- cyclosporine (Neoral, Gengraf, Sandimmune)
- fosamprenavir (Lexiva) with ritonavir
- indinavir (Crixivan)
- ketoconazole (Nizoral)
- nefazodone (Serzone)
- ritonavir (Norvir)
- telithromycin (Ketek)

- clarithromycin (Biaxin)
- darunavir (Prezista)
- fosamprenavir (Lexiva)
- itraconazole (Sporanox)
- lopinavir/ritonavir (Kaletra)
- nelfinavir mesylate (Viracept)
- saquinavir mesylate (Invirase)
- tipranavir (Aptivus)

Ask your healthcare provider or pharmacist if you are not sure if you take any of the medicines listed above. This is not a complete list of all the medicines that can interact with COLCRYS.

- Know the medicines you take. Keep a list of them and show it to your healthcare provider and pharmacist when you get a new medicine.
- Keep COLCRYS out of the reach of children.

What is COLCRYS?

COLCRYS is a prescription medicine used to:

- prevent and treat gout flares in adults
- treat familial Mediterranean fever (FMF) in adults and children age 4 or older

COLCRYS is not a pain medicine, and it should not be taken to treat pain related to other conditions unless specifically prescribed for those conditions.

Who should not take COLCRYS?

Do not take COLCRYS if you have liver or kidney problems and you take certain other medicines. Serious side effects, including death, have been reported in these patients even when taken as directed. See "What is the most important information that I should know about COLCRYS?".

What should I tell my healthcare provider before starting COLCRYS?

See "What is the most important information that I should know about COLCRYS?".

Before you take COLCRYS, tell your healthcare provider about all your medical conditions, including if you:

- have liver or kidney problems.
- are pregnant or plan to become pregnant. It is not known if COLCRYS will harm your unborn baby. Talk to your healthcare provider if you are pregnant or plan to become pregnant.
- are a male with a female partner who can become pregnant. Receiving treatment with COLCRYS may be related to infertility in some men that is reversible when treatment is stopped.
- are breastfeeding or plan to breastfeed. COLCRYS passes into your breast milk. You and your healthcare provider should decide if you will take COLCRYS while breastfeeding. If you take COLCRYS and breastfeed, you should talk to your child's healthcare provider about how to watch for side effects in your child.

Tell your healthcare provider about all the medicines you take, including ones that you may only be taking for a short time, such as antibiotics. See "What is the most important information that I should know about COLCRYS?". Do not start a new medicine without talking to your healthcare provider.

Using COLCRYS with certain other medicines, such as cholesterol-lowering medications and digoxin, can affect each other, causing serious side effects. Your healthcare provider may need to change your dose of COLCRYS. Talk to your healthcare provider about whether the medications you are taking might interact with COLCRYS and what side effects to look for.

How should I take COLCRYS?

- Take COLCRYS exactly as your healthcare provider tells you to take it. If you are not sure about your dosing, call your healthcare provider.
- COLCRYS can be taken with or without food.
- If you take too much COLCRYS, go to the nearest hospital emergency room right away.
- Do not stop taking COLCRYS even if you start to feel better, unless your healthcare provider tells you.
- Your healthcare provider may do blood tests while you take COLCRYS.
- If you take COLCRYS daily and you miss a dose, then take it as soon as you remember. If it is almost time for your next dose, just skip the missed dose. Take the next dose at your regular time. Do not take 2 doses at the same time.
- If you have a gout flare while taking COLCRYS daily, report this to your healthcare provider.

What should I avoid while taking COLCRYS?

Avoid eating grapefruit or drinking grapefruit juice while taking COLCRYS. It can increase your chances of getting serious side effects.

What are the possible side effects of COLCRYS?

COLCRYS can cause serious side effects or even cause death. See "What is the most important information that I should know about COLCRYS?".

Get medical help right away if you have:

- Muscle weakness or pain
- Numbness or tingling in your fingers or toes
- Unusual bleeding or bruising
- Increased infections
- Feel weak or tired
- Pale or gray color to your lips, tongue or palms of your hands
- Severe diarrhea or vomiting

Gout Flares: The most common side effect of COLCRYS in people who have gout flares is diarrhea.

FMF: The most common side effects of COLCRYS in people who have FMF are abdominal pain, diarrhea, nausea and vomiting.

Tell your healthcare provider if you have any side effect that bothers you or that does not go away. These are not all of the possible side effects of COLCRYS. For more information, ask your healthcare provider or pharmacist.

Call your doctor for medical advice about side effects. You may report side effects to FDA at 1-800-FDA-1088.

How should I store COLCRYS?

- Store COLCRYS at room temperature between 68°F and 77°F (20°C and 25°C).
- Keep COLCRYS in a tightly closed container.
- Keep COLCRYS out of the light.

Keep COLCRYS and all medicines out of the reach of children.

General Information about COLCRYS

Medicines are sometimes prescribed for purposes other than those listed in a Medication Guide. Do not use COLCRYS for a condition for which it was not prescribed. Do not give COLCRYS to other people, even if they have the same symptoms that you have. It may harm them. This Medication Guide summarizes the most important information about COLCRYS. If you would like more information, talk with your healthcare provider. You can ask your healthcare provider or pharmacist for information about COLCRYS that is written for healthcare professionals.

What are the ingredients in COLCRYS?

Active Ingredient: colchicine.

Inactive Ingredients: carnauba wax, FD&C blue #2, FD&C red #40, hypromellose, lactose monohydrate, magnesium stearate, microcrystalline cellulose, polydextrose, polyethylene glycol, pregelatinized starch, sodium starch glycolate, titanium dioxide and triacetin.

Distributed by:
Takeda Pharmaceuticals America, Inc.
Lexington, MA 02421

COLCRYS is a trademark of Takeda Pharmaceuticals U.S.A., Inc., registered with the U.S. Patent and Trademark Office and used under license by Takeda Pharmaceuticals America, Inc.
All other trademarks are the property of their respective owners.
For more information, go to www.COLCRYS.com or call 1-877-TAKEDA-7 (1-877-825-3327).

This Medication Guide has been approved by the U.S. Food and Drug Administration
COL243 R4

Revised: May 2020

PRINCIPAL DISPLAY PANEL - 0.6 mg Tablet Bottle Label

30 TABLETS
NDC 64764-119-07

COLCRYS®
(colchicine, USP) tablets
0.6 mg

PHARMACIST:
PLEASE DISPENSE WITH
MEDICATION GUIDE ATTACHED

Takeda
Rx only